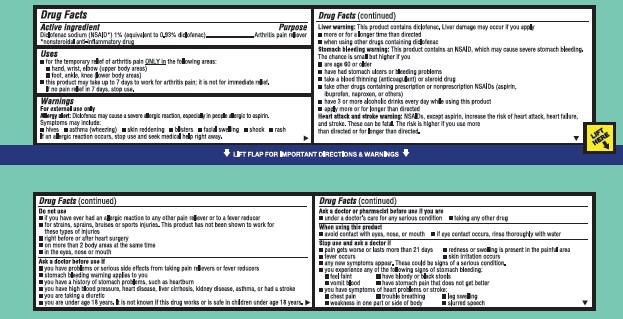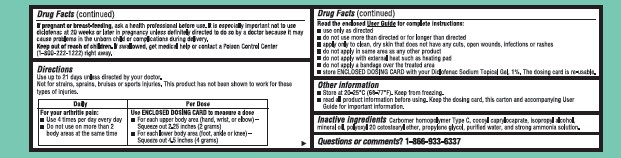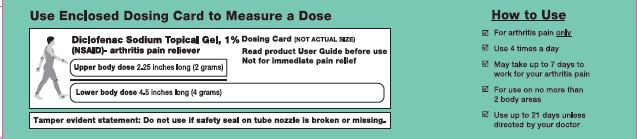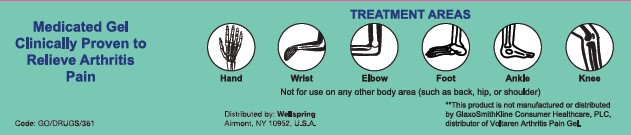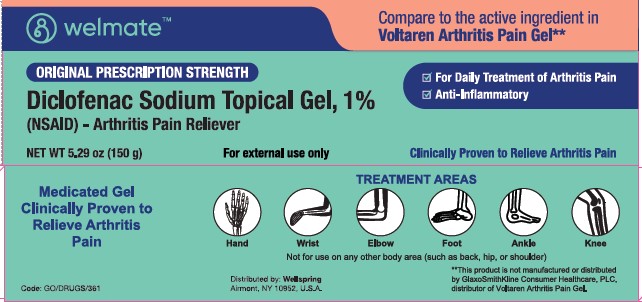 DRUG LABEL: Diclofenac Sodium Topical
NDC: 73581-104 | Form: GEL
Manufacturer: YYBA CORP
Category: otc | Type: HUMAN OTC DRUG LABEL
Date: 20251110

ACTIVE INGREDIENTS: DICLOFENAC SODIUM 1 mg/100 g
INACTIVE INGREDIENTS: WATER; CARBOMER HOMOPOLYMER TYPE C; COCOYL CAPRYLOCAPRATE; ISOPROPYL ALCOHOL; MINERAL OIL; POLYOXYL 20 CETOSTEARYL ETHER; AMMONIA; PROPYLENE GLYCOL

YYBA (as PLD) - Welmate Diclofenac Sodium Topical Gel, 1% (73581-104)

Active ingredient

DICLOFENAC SODIUM (NSAID*) 1% (EQUIVALENT TO 0.93% DICLOFENAC)

*NONSTEROIDAL ANTI-INFLAMMATORY DRUG

Purpose

ARTHRITIS PAIN RELIEVER

Uses

- FOR THE TEMPORARY RELIEF OF ARTHRITIS PAIN ONLY IN THE FOLLOWING AREAS:
- HAND, WRIST, ELBOW (UPPER BODY AREAS)
- FOOT, ANKLE, KNEWW (LOWER BODY AREAS)
- THIS PRODUCT MAY TAKE UP TO 7 DAYS TO WORK FOR ARTHRITIS PAIN; IT IS NOT FOR IMMEDIATE RELIEF. IF NO PAIN IN 7 DAYS, STOP USE.

Warnings

FOR EXTERNAL USE ONLY.

ALLERGY ALERT: DICLOFENAC MAY CAUSE A SEVERE ALLERGIC REACTION, ESPECIALLY IN PEOPLE ALLERGIC TO ASPIRIN. SYMPROMS MAY INCLUDE:

- HIVES
- ASTHMA (WHEEZING)
- SKIN REDDENING
- BLISTERS
- FACIAL SWELLING
- SHOCK
- RASH

IF ALLERGIC REACTION OCCURS, STOP USING AND SEEK MEDICAL HELP RIGHT AWAY.

LIVER WARNING: THIS PRODUCT CONTAINS DICLOFENAC. LIVER DAMAGE MAY OCCUR IF YOU APPLY

- MORE OR FOR A LONGER TIME THAN DIRECTED.
- WHEN USING OTHER DRUGS CONTAINING DICLOFENAC

STOMACH BLEEDING WARNING: THIS PRODUCT CONTAINS AN NSAID, WHICH MAY CAUSE SEVERE STOMACH BLEEDING. THE CHANCE IS SMALL BUT HIGHER IF YOU

- ARE AGE 60 OR OLDER
- HAVE HAD STOMACH ULCERS OR BLEEDING PROBLEMS
- TAKE A BLOOD THINNING (ANTICOAGULANT) OR STEAROID DRUGS
- TAKE OTHER DRUGS CONTAINING PRESCRIPTION OR NONPRESCRIPTION NSAIDS (ASPIRIN, IBUPROFEN, NAPROXEN, OR OTHERS)
- HAVE 3 OR MORE ALCOHOLIC DRINKS EVERY DAY WHILE USING THIS PRODUCT
- APPLY MORE OR FOR LONGER THAN DIRECTED

HEART ATTACK AND STROKE WARNING: NSAIDS, EXCEPT ASPIRIN, INCREASE THE RISK OF HEART ATTACK, HEART FAILURE, AND STROKE. THESE CAN BE FATAL. THE RISK IS HIGHER IF YOU USE MORE THAN DIRECTED OR FOR LONGER THAN DIRECTED.

DO NOT USE

- IF YOU HAVE EVER HAD AN ALLERGIC REACTION TO ANY OTHER PAIN RELIEVER OR TO A FEVER REDUCER
- FOR STRAINS, SPRAINS, BRUISES OR SPORTS INJURIES. THIS PRODUCT HAS NOT BEEN SHOWN TO WORK FOR THESE TYPES OF INJUTIRES
- RIGHT BEFORE OR AFTER HEART SURGERY
- ON MORE THAN 2 BODY AREAS AT THE SAME TIME
- IN THE EYES, NOSE OR MOUTH

ASK A DOCTOR BEFORE USE IF

- YOU HAVE PROBLEMS OR SERIOUS SIDE EFFECTS FROM TAKING PAIN RELIEVERS OR FEVER REDUCERS
- STOMACH BLEEDING WARNING APPLIES TO YOU
- YOU HAVE A HISTORY OF STOMACH PROBLEMS, SUCH AS HEARTBURN
- YOU HAVE HIGH BLOOD PRESSURE, HEART DISEASE, LIVER CIRRHOSIS, KIDNEY DISEASE, ASTHMA, OR HAD A STROKE
- YOU ARE TAKING A DIURETIC
- YOU ARE UNDER AGE 18 YEARS. IT IS NOT KNOWN IF THIS DRUG WORKS OR IS SAFE IN CHILDREN UNDER AGE 18 YEARS.

ASK A DOCTOR OR PHARMACIST BEFORE USE IF YOU ARE

- UNDER A DOCTOR'S CARE FOR ANY SERIOUS CONDITION
- TAKING ANY OTHER DRUG

WHEN USING THIS PRODUCT

- AVOID CONTACT WITH EYES, NOSE, OR MOUTH
- IF EYE CONTACT OCCURS, RINSE THOROUGHLY WITH WATER

STOP USE AND ASK A DOCTOR IF

- PAIN GETS WORSE OR LASTS MORE THAN 21 DAYS
- REDNESS OR SWELLING IS PRESENT IN THE PAINFUL AREA
- FEVER OCCURS
- SKIN IRRITATION OCCURS
- ANY NEW SYMPTOMS APPEAR. THESE COULD BE SIGNS OF A SERIOUS CONDITION.
- YOU EXPERIENCE ANY OF THE FOLLOWING SIGNS OF STOMACH BLEEDING:
- FEEL FAINT
- HAVE BLOODY OR BLACK STOOLS
- VOMIT BLOOD
- HAVE STOMACH PAIN THAT DOES NOT GET BETTER
- IF YOU HAVE SYMPTOMS OF HEART PROBLEMS OR STROKE:
- CHEST PAIN
- TROUBLE BREATHING
- LEG SWELLING
- WEAKNESS IN ONE PART OR SIDE OF BODY
- SLURRED SPEECH

IF PREGNANT OR BREAST-FEEDING, ASK A HEALTH PROFESSIONAL BEFORE USE. IT IS ESPECIALLY IMPORTANT NOT TO USE DICLOFENAC AT 20 WEEKS OR LATER IN PREGNANCY UNLESS DEFINITELY DIRECTED TO DO SO BY A DOCTOR BECAUSE IT MAY CAUSE PROBLEMS IN THE UNBORN CHILD OR COMPLICATIONS DURING DELIVERY.

KEEP OUT OF REACH OF CHILDREN. IF SWALLOWED, GET MEDICAL HELP OR CONTACT A POISON CONTROL CENTER (1-800-222-1222) RIGHT AWAY.

Directions

USE UP TO 21 DAYS UNLESS DIRECTED BY YOUR DOCTOR.

NOT FOR STRAINS, SPRAINS, BRUISES, OR SPORTS INJURIES. THIS PRODUCT HAS NOT BEEN SHOWN TO WORK FOR THESE TYPES OF INJURIES.

DAILY | PER DOSE
FOR YOUR ARTHRITIS PAIN:; - USE 4 TIMES PER DAY EVERY DAY - DO NOT USE ON MORE THAN 2 BODY AREAS AT THE SAME TIME | USE ENCLOSED DOSING CARD TO MEASURE A DOSE; - FOR EACH UPPER BODY AREA (HAND, WRIST, OR ELBOW) - SQUEEZE OUT 2.25 INCHES (2 GRAMS) - FOR EACH LOWER BODY AREA (FOOT ANKLE, OR KNEE) - SQUEEZE OUT 4.5 INCHES (4 GRAMS)

READ THE ENCLOSED USER GUIDE FOR COMPLETE INSTRUCTIONS:

- USE ONLY AS DIRECTED
- DO NOT USE MORE THAN DIRECTED OR FOR LONGER THAN DIRECTED
- APPLY ONLY TO CLEAN, DRY SKIN THAT DOES NOT HAVE ANY CUTS, OPEN WOUNDS, INFECTIONS, OR RASHES
- DO NOT APPLY IN SAME AREA AS ANY OTHER PRODUCT
- DO NOT APPLY WITH EXTERNAL HEAT SUCH AS A HEATING PAD
- DO NOT APPLY A BANDAGE OVER THE TREATED AREA
- STORE ENCLOSED DOSING CARD WITH YOUR DICLOFENAC SODIUM TOPICAL GEL, 1%. tHE DOSING CARD IS RE-USABLE.

OTHER INFORMATION

- STORE AT 20-25°C (68-77°F). KEEP FROM FREEZING.
- READ ALL PRODUCT INFORMATION BEFORE USING. KEEP THE DOSING CARD, THIS CARTON AND ACCOMPANYING USER GUIDE FOR IMPORTANT INFORMATION.

INACTIVE INGREDIENTS

CARBOMER HOMOPOLYMER TYPE C, COCOYL CAPRYLOCAPRATE, ISOPROPYL ALCOHOL, MINERAL OIL, POLYOXYL 20 CETOSTEARYL ETHER, PROPYLENE GLYCOL, PURIFIED WATER, AND STRONG AMMONIA SOLUTION.

QUESTIONS OR COMMENTS?

1-866-933-6337